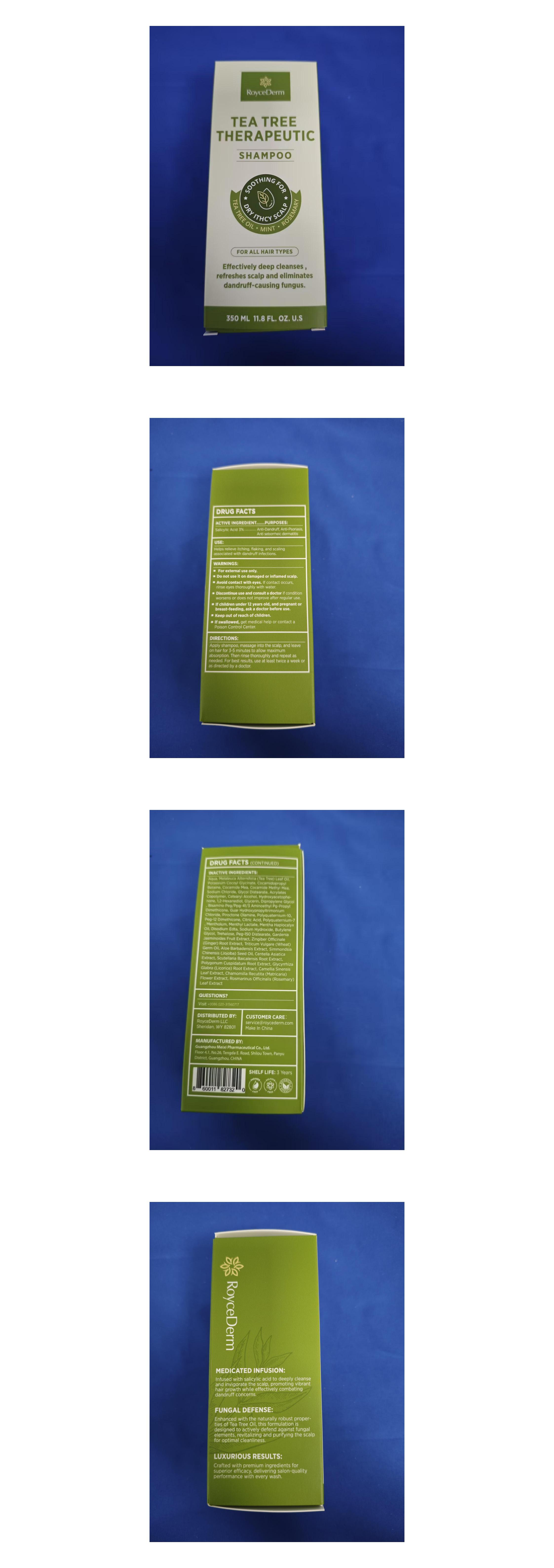 DRUG LABEL: RoyceDerm Tea Tree Therapeutic
NDC: 84710-101 | Form: LOTION/SHAMPOO
Manufacturer: Guangzhou Meixi Pharmaceuticals Co., Ltd.
Category: otc | Type: HUMAN OTC DRUG LABEL
Date: 20240912

ACTIVE INGREDIENTS: SALICYLIC ACID 10.5 g/350 g
INACTIVE INGREDIENTS: MENTHYL LACTATE, (-)-; COCAMIDOPROPYL BETAINE; HYDROXYACETOPHENONE; DIPROPYLENE GLYCOL; COCO MONOETHANOLAMIDE; SODIUM CHLORIDE; BUTYL ACRYLATE/METHYL METHACRYLATE/METHACRYLIC ACID COPOLYMER (18000 MW); 1,2-HEXANEDIOL; TREHALOSE; BUTYLENE GLYCOL; COCOYL METHYL MONOETHANOLAMINE; ALOE VERA LEAF; POTASSIUM COCOYL GLYCINATE; PEG-12 DIMETHICONE; CITRIC ACID MONOHYDRATE; POLYQUATERNIUM-7 (70/30 ACRYLAMIDE/DADMAC; 1600 KD); MENTHA ARVENSIS LEAF OIL; EDETATE DISODIUM; SODIUM HYDROXIDE; PEG-150 DISTEARATE; GARDENIA JASMINOIDES FRUIT; GINGER; WHEAT GERM OIL; CENTELLA ASIATICA TRITERPENOIDS; SCUTELLARIA BAICALENSIS ROOT; POLYGONUM CUSPIDATUM ROOT; GLYCYRRHIZA GLABRA; GREEN TEA LEAF; CHAMOMILE; PIROCTONE OLAMINE; POLYQUATERNIUM-10 (10000 MPA.S AT 2%); METHOXY PEG/PPG-7/3 AMINOPROPYL DIMETHICONE; MELALEUCA ALTERNIFOLIA (TEA TREE) LEAF OIL; GLYCOL DISTEARATE; CETOSTEARYL ALCOHOL; MENTHOL, UNSPECIFIED FORM; JOJOBA OIL; WATER; GLYCERIN; GUAR HYDROXYPROPYLTRIMONIUM CHLORIDE; ROSEMARY

Active Ingredient: Salicylic Acid 3%

Purpose: Anti-Dandruff, Anti-Psoriasis, Anti seborrheic dermatitis

INDICATIONS AND USAGE

Use: Helps relieve itching, flaking, and scaling associated with dandruff infections.

Warnings:

For external use only.

Do not use it on damaged or inflamed scalp.

Avoid contact with eyes. If contact occurs, rinse eyes thoroughly with water.

Discontinue use and consult a doctor if condition worsens or does not improve after regular use.

If children under 12 years old, and pregnant or breast-feeding, ask a doctor before use.

Keep out of reach of children.
If swallowed, get medical help or contact a Poison Control Center.

Directions:

Apply shampoo, massage into the scalp, and leave on hair for 3-5 minutes to allow maximum absorption. Then rinse thoroughly and repeat as needed. For best results, use at least twice a week or as directed by a doctor.

Shelf Life: 3 Years

INACTIVE INGREDIENT

Inactive Ingredients: Aqua, Melaleuca Alternifolia (Tea Tree) Leaf Oil, Potassium Cocoyl Glycinate, Cocamidopropyl Betaine, Cocamide Mea, Cocamide Methyl Mea, Sodium Chloride, Glycol Distearate, Acrylates Copolymer, Cetearyl Alcohol, Hydroxyacetophenone, 1,2-Hexanediol, Glycerin, Dipropylene Glycol, Bisamino Peg/Ppg-41/3 Aminoethyl Pg-Propyl Dimethicone, Guar Hydroxypropyltrimonium Chloride, Piroctone Olamine, Polyquaternium-10, Peg-12 Dimethicone, Citric Acid, Polyquaternium-7, Mentholum, Menthyl Lactate, Mentha Haplocalyx Oil, Disodium Edta, Sodium Hydroxide, Butylene Glycol, Trehalose, Peg-150 Distearate, Gardenia jasminoides Fruit Extract, Zingiber Officinale(Ginger)Root Extract, Triticum Vulgare(Wheat)Germ Oil, Aloe Barbadensis Extract, Simmondsia Chinensis(Jojoba)Seed Oil, Centella Asiatica Extract, Scutellaria Baicalensis Root Extract, Polygonum Cuspidatum Root Extract, Glycyrrhiza Glabra(Licorice)Root Extract, Camellia Sinensis Leaf Extract, Chamomilla Recutita(Matricaria)Flower Extract, Rosmarinus Officinalis (Rosemary) Leaf Extract

Questions?
Visit www.roycederm.com

+1 307 461 0958

Customer care: service@roycederm.com

STATEMENT OF IDENTITY

Distributed by:

RoyceDerm LLC

Sheridan, WY 82801

MANUFACTURED BY:

Guangzhou Meixi Pharmaceuticals Co., Ltd.

Floor 4, 1, No.26, Tengda E. Road, Shilou Town, Panyu District, Guangzhou, CHINA

Label